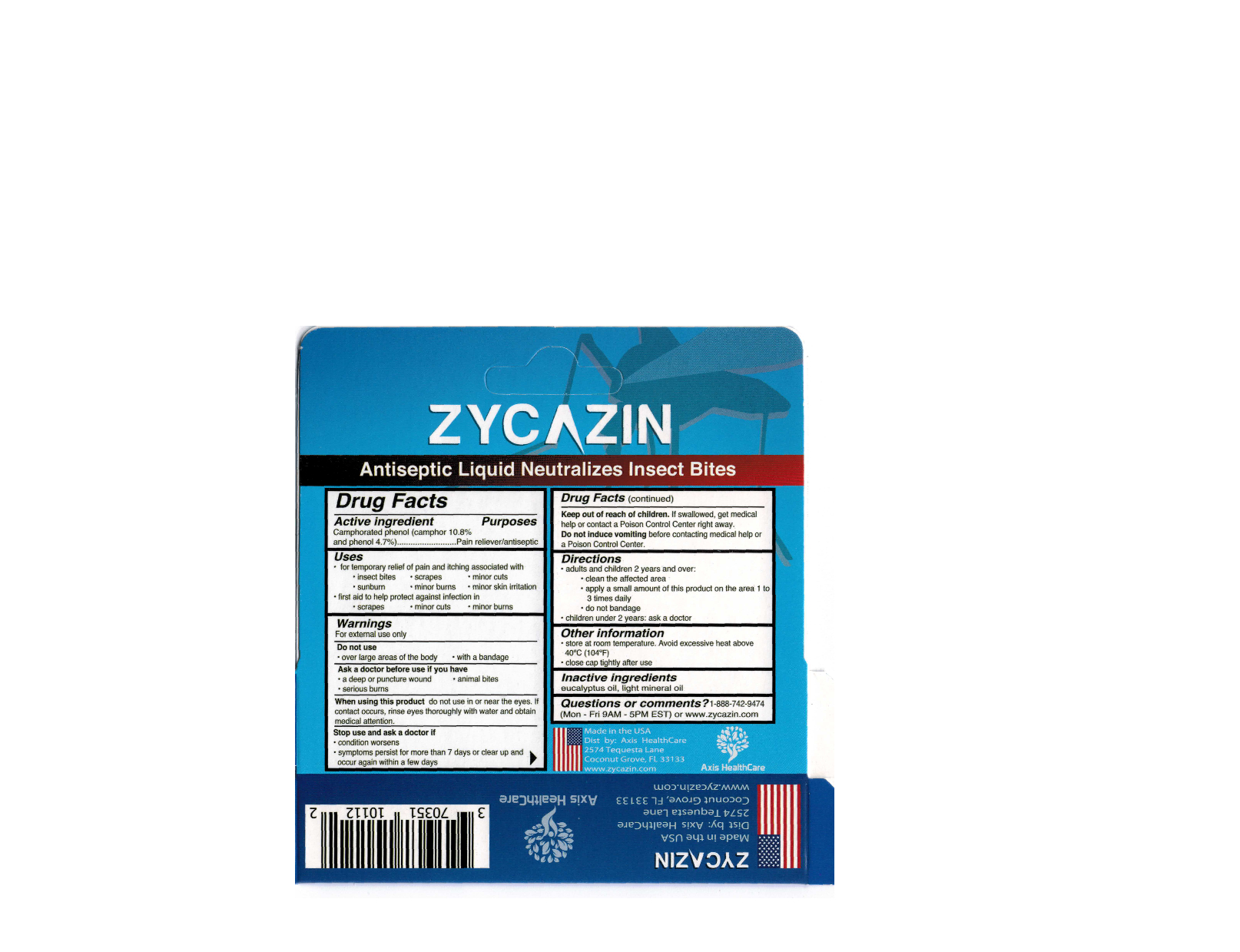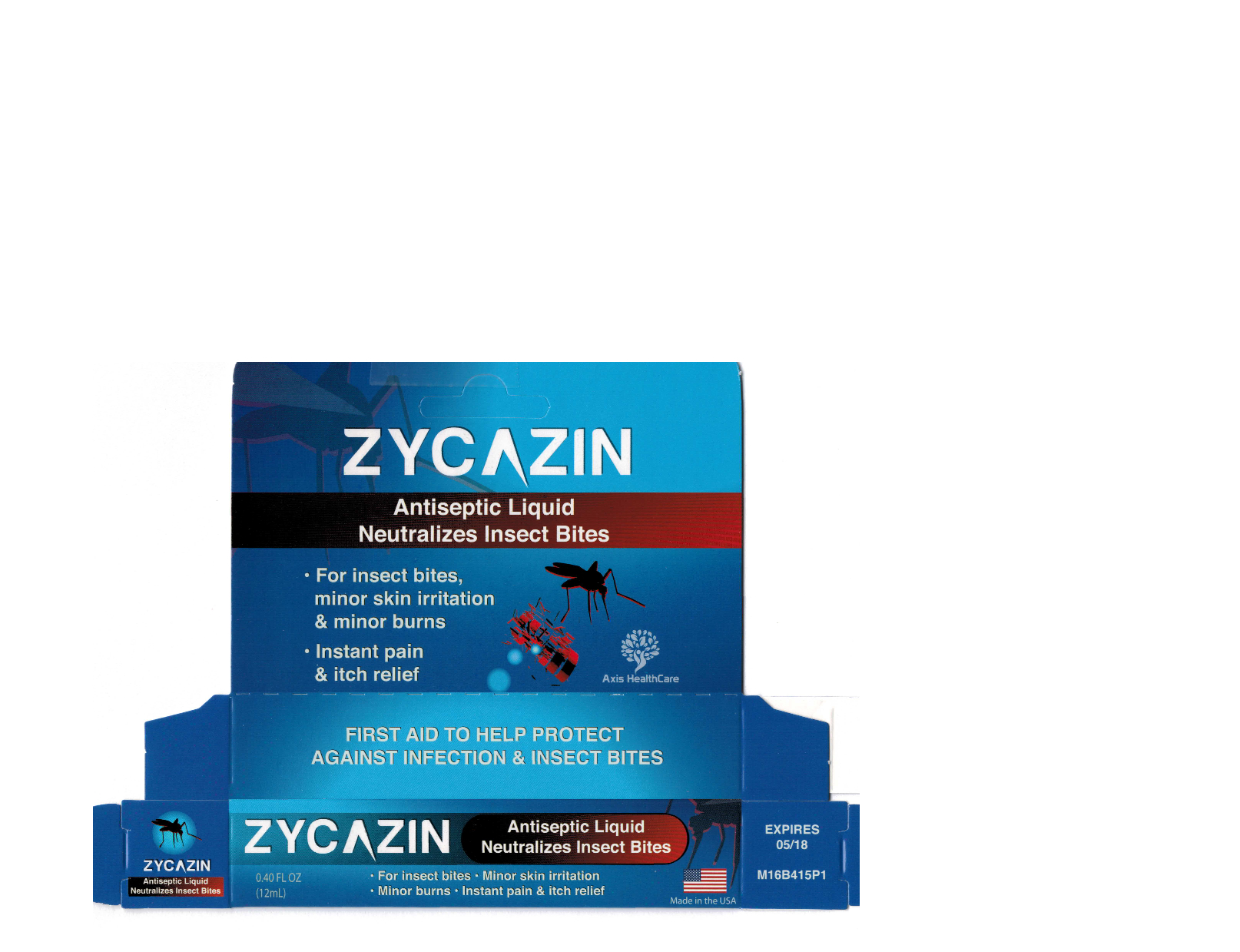 DRUG LABEL: ZYCAZIN Antiseptic Liquid
NDC: 70351-101 | Form: LIQUID
Manufacturer: Axis Scientific LLC
Category: otc | Type: HUMAN OTC DRUG LABEL
Date: 20161023

ACTIVE INGREDIENTS: CAMPHOR (NATURAL) 10.8 mg/100 mL; PHENOL 4.7 mg/100 mL
INACTIVE INGREDIENTS: LIGHT MINERAL OIL; EUCALYPTUS OIL

ZYCAZIN Antiseptic Liquid

Active ingredient

Camphorated phenol (camphor 10.8% and phenol 4.7%)

Purposes

Pain reliever/antiseptic

Uses

- for temporary relief of pain associated with

insect bites, minor burns, sunburn, minior cuts, scrapes, minor skin irritation, cold sores

- first aid to help protect against infection in

minor cuts, scrapes, minor burns

Warnings

For external use only

Do not use

- over large areas of the body
- with a bandage

Ask a doctor before use if you have

- a deep or puncture wound
- animal bites
- serious burns

When using this product

do not use in or near the eyes. If contact occurs, rinse eyes thoroughly with water and obtain medical attention.

Stop use and ask a doctor if

- condition worsens
- symptoms persis for more than 7 days or clear up and occur again within a few days

Keep out of reach of children.

If swallowed, get medical help or contact a Poison Control Center right away.

Do not induce vomiting before contacting medical help or a Poison Control Center.

Directions

- adults and children 2 years and over:
- clean the affected area
- apply a small amount of this product on the area 1 to 3 times daily
- do not bandage
- children under 2 years: ask a doctor

Other information

- store at room temperature. Avoid excessive heat above 40°C (104°F).
- close cap tightly after use

Inactive ingredients

eucalyptus oil, light mineral oil

Questions or comments?

1-888-742-9474 (Mon - Fri 9AM - 5PM EST) or www.zycazin.com

Carton

Carton front